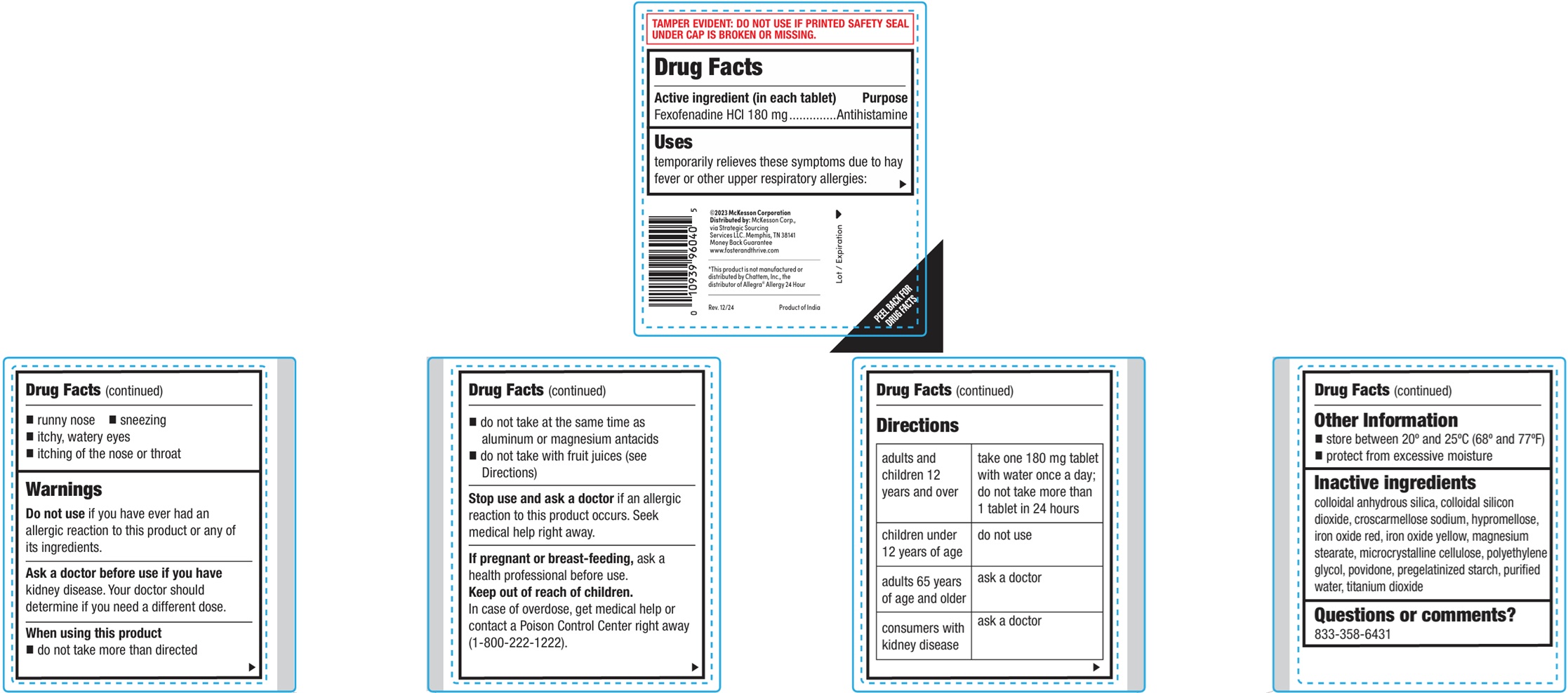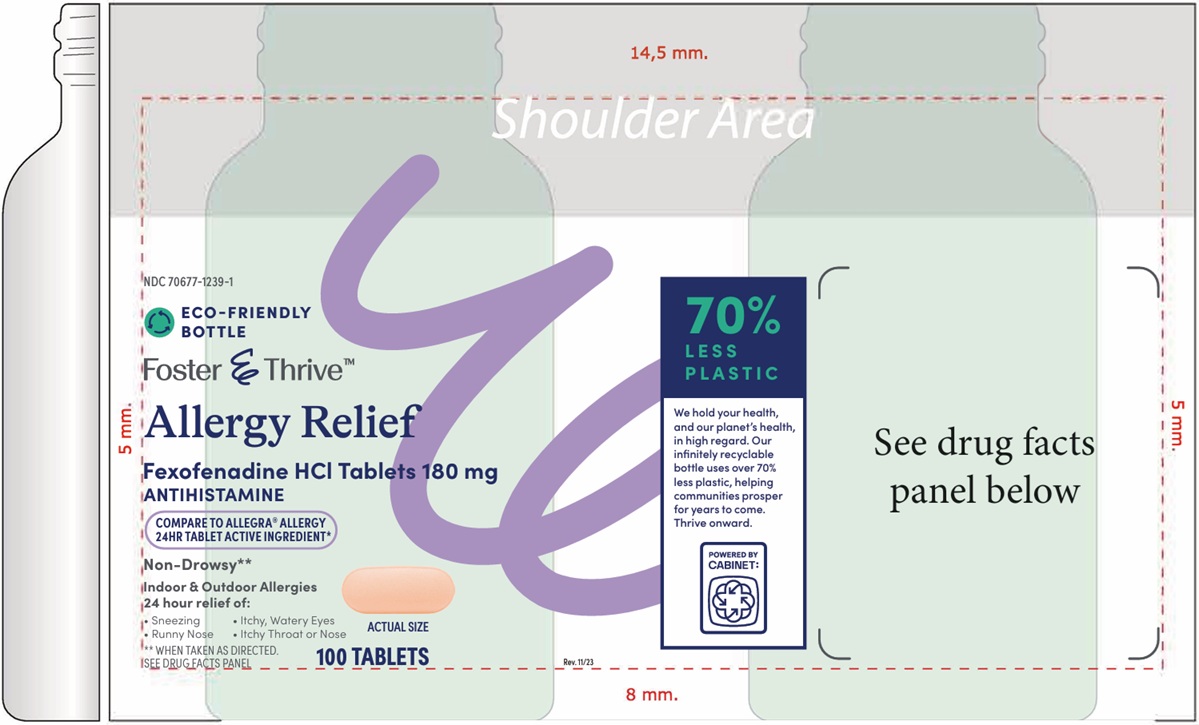 DRUG LABEL: FEXOFENADINE HCl
NDC: 70677-1239 | Form: TABLET, FILM COATED
Manufacturer: Strategic Sourcing Services, LLC
Category: otc | Type: HUMAN OTC DRUG LABEL
Date: 20260129

ACTIVE INGREDIENTS: FEXOFENADINE HYDROCHLORIDE 180 mg/1 1
INACTIVE INGREDIENTS: SILICON DIOXIDE; CROSCARMELLOSE SODIUM; HYPROMELLOSE, UNSPECIFIED; FERRIC OXIDE RED; FERRIC OXIDE YELLOW; MAGNESIUM STEARATE; MICROCRYSTALLINE CELLULOSE; POLYETHYLENE GLYCOL, UNSPECIFIED; POVIDONE; STARCH, CORN; WATER; TITANIUM DIOXIDE

Fexofenadine HCl Tablets, 180 mg
ANTIHISTAMINE